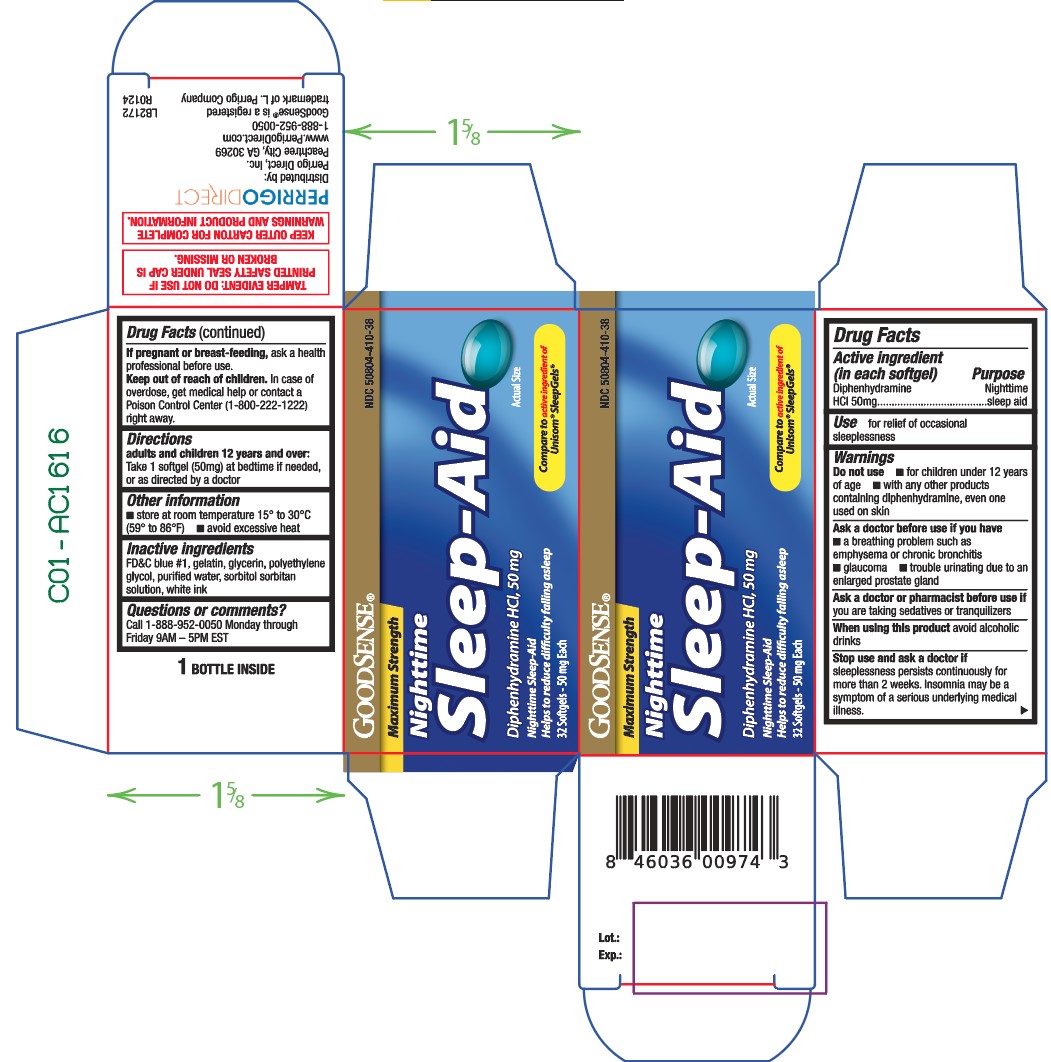 DRUG LABEL: Sleep Aid
NDC: 50804-410 | Form: CAPSULE, LIQUID FILLED
Manufacturer: Good Sense
Category: otc | Type: HUMAN OTC DRUG LABEL
Date: 20240618

ACTIVE INGREDIENTS: DIPHENHYDRAMINE HYDROCHLORIDE 50 mg/1 1
INACTIVE INGREDIENTS: FD&C BLUE NO. 1; GELATIN; GLYCERIN; POLYETHYLENE GLYCOL, UNSPECIFIED; WATER; SORBITOL SOLUTION

410 - Nighttime Sleep Aid

Active ingredient(s)

Diphenhydramine HCl 50mg

Purpose

Nighttime sleep aid

Use(s)

- for relief of occasional sleeplessness

Warnings

Do not use

- for children under 12 years of age
- with any other products containing diphenhydramine, even one used on skin

Ask a doctor before use if

- a breathing problem such as emphysema or chronic bronchitis
- glaucoma
- trouble urinating due to an enlarged prostate gland

Ask a doctor or pharmacist before use if

you are taking sedatives or tranquilizers

When using this product

avoid alcoholic drinks

Stop use and ask a doctor if

sleeplessness persists continuously for more than 2 weeks. Insomnia may be a symptom of a serious underlying medical illness.

If pregnant or breastfeeding,

ask a health professional before use.

Keep out of reach of children

In case of overdose, get medical help or contact a Poison Control Center (1-800-222-1222) right away.

Directions

Adults and children 12 years and over: 1 softgel (50mg) at bedtime if needed, or as directed by a doctor

Other information

- store at room temperature 15° to 30°C (59° to 86°F)
- avoid excessive heat

Inactive ingredients

FD&C blue #1, gelatin, glycerin, polyethylene glycol, purified water, sorbitol sorbitan solution, white ink

Questions/Comments

Call 1-888-952-0050 Monday through Friday 9AM – 5PM EST

Principal Display Panel

Sleep Aid